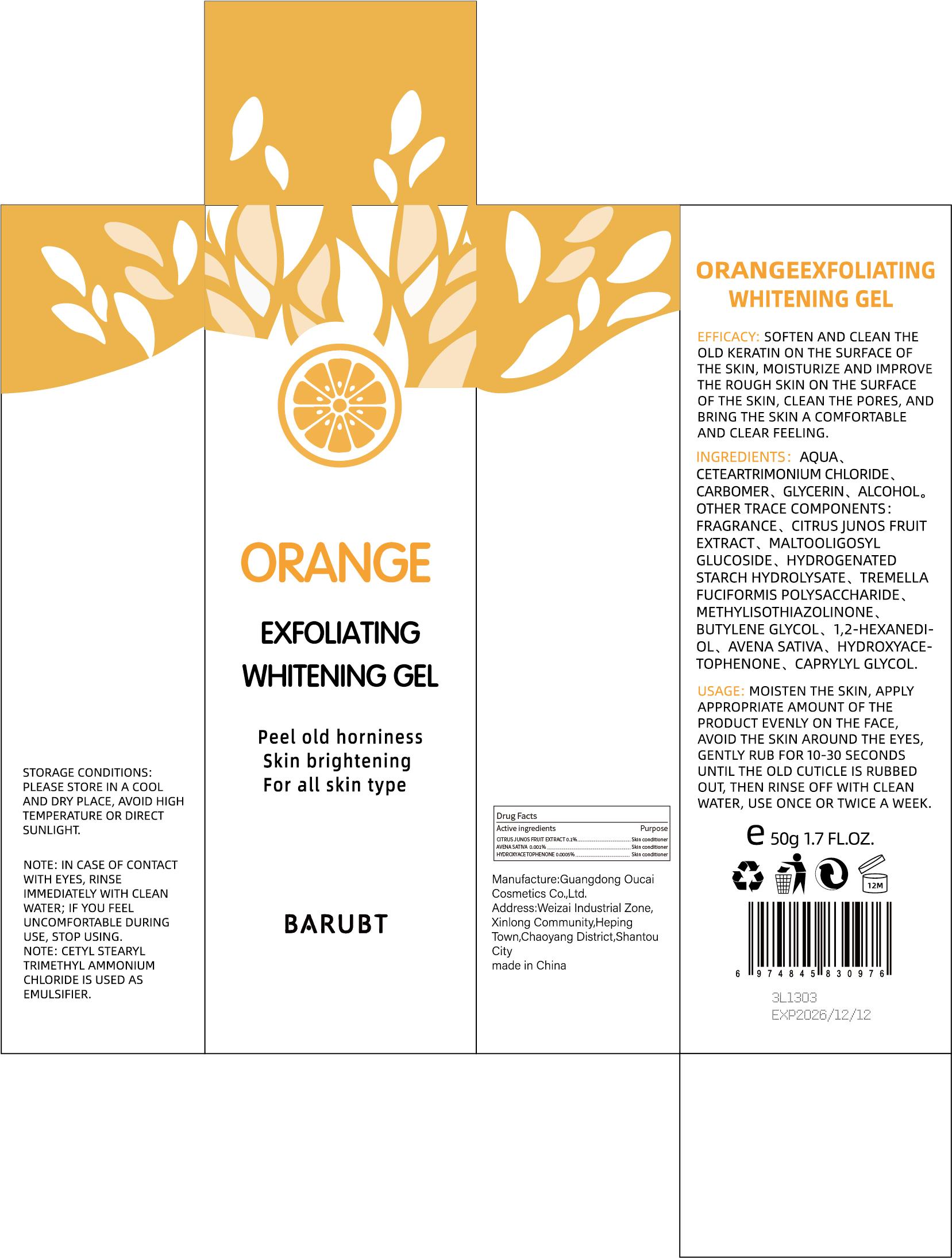 DRUG LABEL: BARUBT Orange Exfoliating Whitening Gel
NDC: 84712-020 | Form: GEL
Manufacturer: Guangdong Youbaijia Cosmetic Industry Co., Ltd
Category: otc | Type: HUMAN OTC DRUG LABEL
Date: 20240918

ACTIVE INGREDIENTS: HYDROXYACETOPHENONE 0.00025 g/50 g; CITRUS JUNOS FRUIT 0.05 g/50 g; AVENA SATIVA WHOLE 0.0005 g/50 g
INACTIVE INGREDIENTS: GLYCERIN 1 g/50 g; CETEARTRIMONIUM CHLORIDE 1.05 g/50 g

ACTIVE INGREDIENT

CITRUS JUNOS FRUIT EXTRACT 0.1%
AVENA SATIVA 0.001%
HYDROXYACETOPHENONE 0.0005%

INACTIVE INGREDIENT

AQUA
CETEARTRIMONIUM CHLORIDE
CARBOMER
GLYCERIN
ALCOHOL
FRAGRANCE
MALTOOLIGOSYLGLUCOSIDE
HYDROGENATED STARCH HYDROLYSATE
TREMELLA FUCIFORMIS POLYSACCHARIDE
METHYLISOTHIAZOLINONE
BUTYLENE GLYCOL
1,2-HEXANEDIOL
CAPRYLYL GLYCOL

Do not use on damaged skin.

Keep away from children. Do not swallow.

PURPOSE

EXFOLIATING WHITENING GEL

QUESTIONS

Contact name: Jessie Peng
Company phone number: +1 818 579 7288
Company e-mail: jessie@registeragentllc.com

STOP USE

lf skin becomes red or irritated, discontinue use immediately and wash with water.

WHEN USING

keep out of eyes. Rinse with water to remove.

WARNINGS

For external use only.

STORAGE AND HANDLING

Keep away from light and in a dry place.

INDICATIONS AND USAGE

SOFTEN AND CLEAN THE OLD KERATIN ON THE SURFACE OF THE SKIN, MOISTURIZE AND IMPROVE THE ROUGH SKIN ON THE SURFACE OF THE SKIN, CLEAN THE PORES, AND BRING THE SKIN A COMFORTABLE AND CLEAR FEELING.

DOSAGE AND ADMINISTRATION

MOISTEN THE SKIN, APPLY APPROPRIATE AMOUNT OF THE PRODUCT EVENLY ON THE FACE,AVOID THE SKIN AROUND THE EYES,GENTLY RUB FOR 10-30 SECONDS UNTIL THE OLD CUTICLE IS RUBBED OUT, THEN RINSE OFF WITH CLEAN WATER, USE ONCE OR TWICE A WEEK,